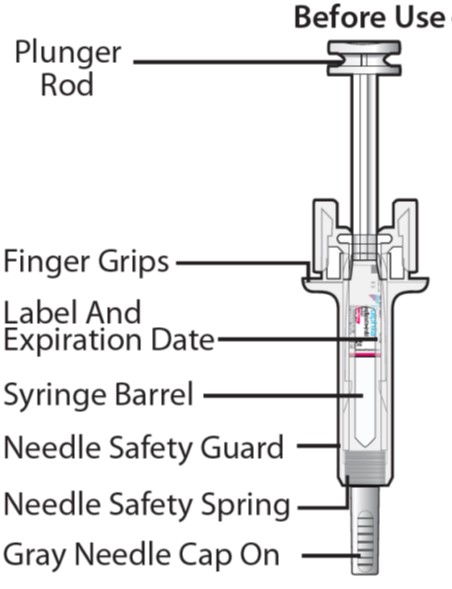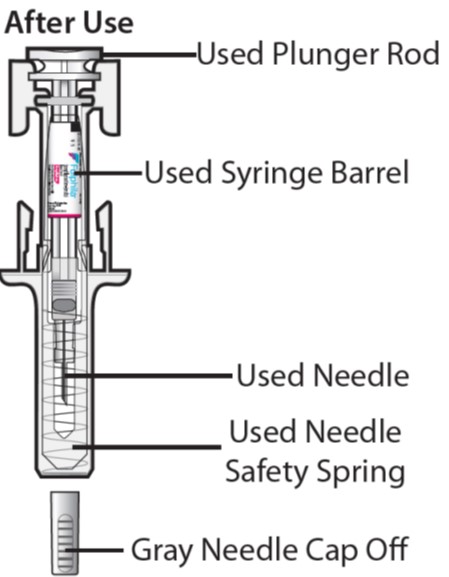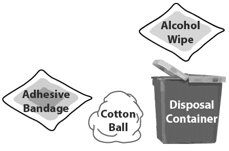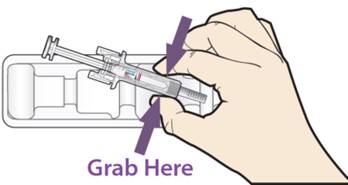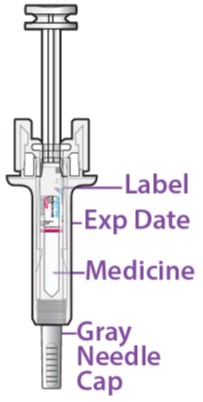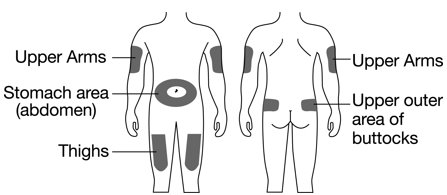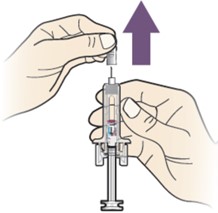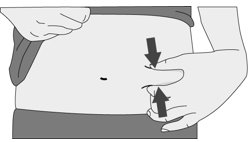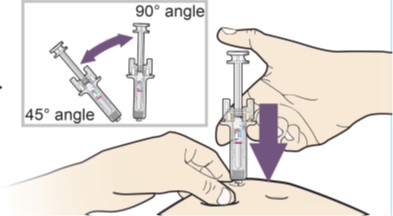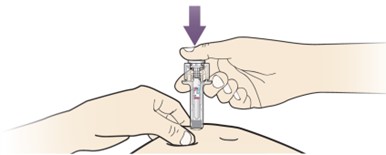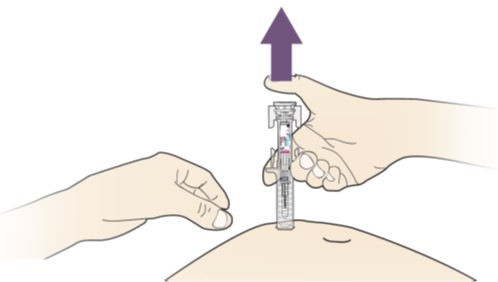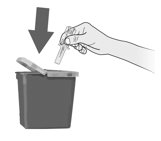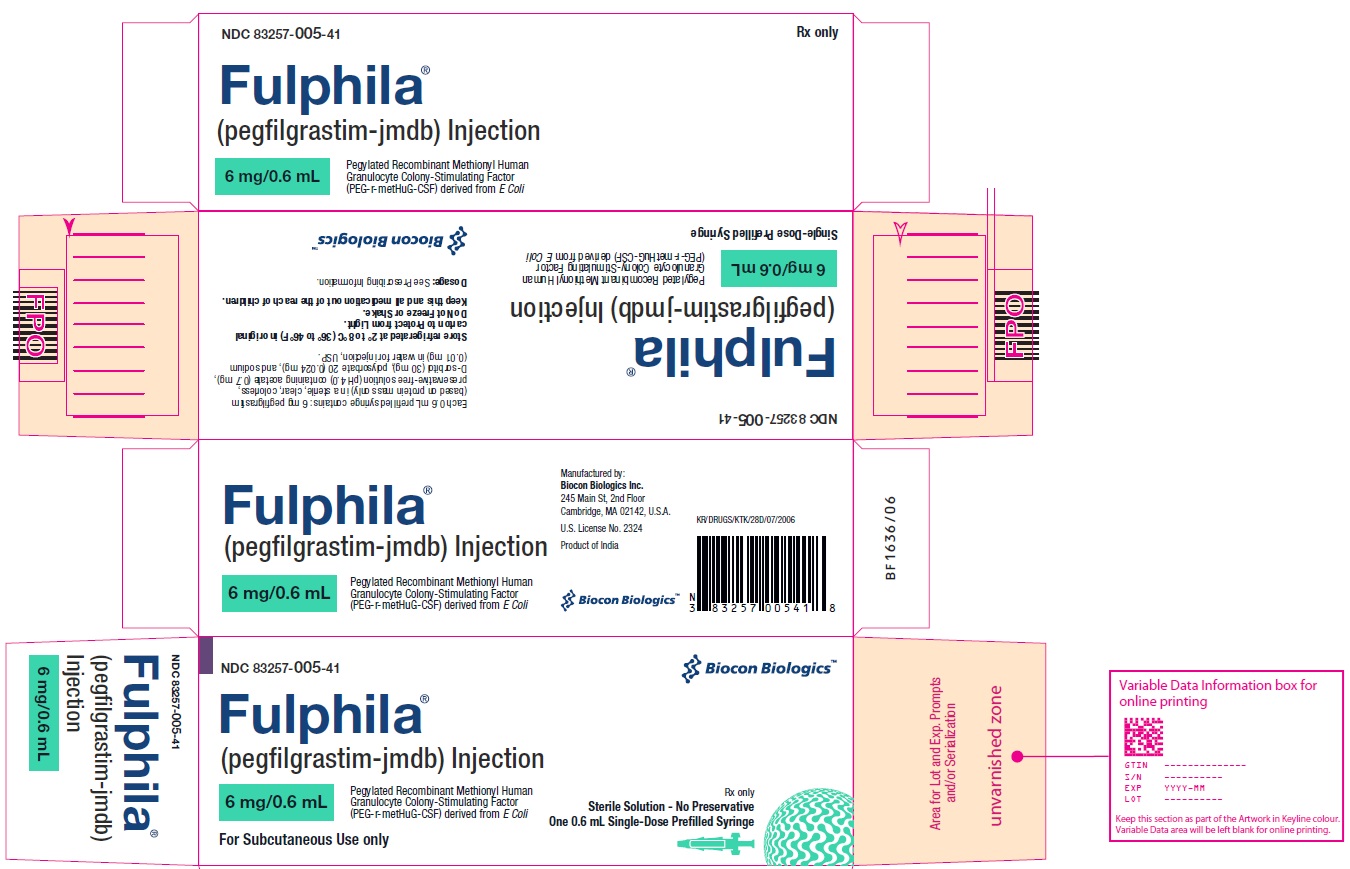 DRUG LABEL: Fulphila
NDC: 83257-005 | Form: INJECTION
Manufacturer: Biocon Biologics Inc.
Category: prescription | Type: HUMAN PRESCRIPTION DRUG LABEL
Date: 20231205

ACTIVE INGREDIENTS: PEGFILGRASTIM 6 mg/0.6 mL
INACTIVE INGREDIENTS: ACETIC ACID; POLYSORBATE 20; SODIUM HYDROXIDE; SORBITOL; WATER

HIGHLIGHTS OF PRESCRIBING INFORMATION

These highlights do not include all the information needed to use FULPHILA safely and effectively. See full prescribing information for FULPHILA.
FULPHILA® (pegfilgrastim-jmdb) injection, for subcutaneous use
Initial U.S. Approval: 2018
FULPHILA® (pegfilgrastim-jmdb) is biosimilar* to NEULASTA® (pegfilgrastim). (1)

RECENT MAJOR CHANGES

Warnings and Precautions, Thrombocytopenia (5.7) 03/2021

Warnings and Precautions, Myelodysplastic Syndrome (MDS) and Acute Myeloid Leukemia (AML) (5.10) 03/2021

1 INDICATIONS AND USAGE

Fulphila is a leukocyte growth factor indicated to

- Decrease the incidence of infection, as manifested by febrile neutropenia, in patients with non-myeloid malignancies receiving myelosuppressive anti-cancer drugs associated with a clinically significant incidence of febrile neutropenia. (1.1)

Limitations of Use

Fulphila is not indicated for the mobilization of peripheral blood progenitor cells for hematopoietic stem cell transplantation.

2 DOSAGE AND ADMINISTRATION

- Patients with cancer receiving myelosuppressive chemotherapy
  - 6 mg administered subcutaneously once per chemotherapy cycle. (2.1)
  - Do not administer between 14 days before and 24 hours after administration of cytotoxic chemotherapy. (2.1)
  - Use weight based dosing for pediatric patients weighing less than 45 kg; refer to Table 1. (2.2)

3 DOSAGE FORMS AND STRENGTHS

- Injection: 6 mg/0.6 mL solution in a single-dose prefilled syringe for manual use only. (3)

4 CONTRAINDICATIONS

Patients with a history of serious allergic reactions to human granulocyte colony-stimulating factors such as pegfilgrastim products or filgrastim products. (4)

5 WARNINGS AND PRECAUTIONS

- Fatal splenic rupture: Evaluate patients who report left upper abdominal or shoulder pain for an enlarged spleen or splenic rupture. (5.1)
- Acute respiratory distress syndrome (ARDS): Evaluate patients who develop fever, lung infiltrates, or respiratory distress. Discontinue Fulphila in patients with ARDS. (5.2)
- Serious allergic reactions, including anaphylaxis: Permanently discontinue Fulphila in patients with serious allergic reactions. (5.3)
- Fatal sickle cell crises: Discontinue Fulphila if sickle cell crisis occurs. (5.4)
- Glomerulonephritis: Evaluate and consider dose-reduction or interruption of Fulphila if causality is likely. (5.5)
- Thrombocytopenia: Monitor platelet counts. (5.7)
- Myelodysplastic Syndrome (MDS) and Acute Myeloid Leukemia (AML): Monitor patients with breast and lung cancer using Fulphila in conjunction with chemotherapy and/or radiotherapy for signs and symptoms of MDS/AML. (5.10)

6 ADVERSE REACTIONS

Most common adverse reactions (≥ 5% difference in incidence compared to placebo) are bone pain and pain in extremity. (6.1)

To report SUSPECTED ADVERSE REACTIONS, contact Biocon Biologics Inc. at 1-833-986-1468 (1-877-4-INFO-RX) or FDA at 1-800-FDA-1088 or www.fda.gov/medwatch.

*Biosimilar means that the biological product is approved based on data demonstrating that it is highly similar to an FDA-approved biological product, known as a reference product, and that there are no clinically meaningful differences between the biosimilar product and the reference product.

Biosimilarity of Fulphila has been demonstrated for the condition(s) of use (e.g. indication(s), dosing regimen(s)), strength(s), dosage form(s), and route(s) of administration described in its Full Prescribing Information.

FULL PRESCRIBING INFORMATION

1 INDICATIONS AND USAGE

1.1 Patients with Cancer Receiving Myelosuppressive Chemotherapy

Fulphila is indicated to decrease the incidence of infection, as manifested by febrile neutropenia, in patients with non-myeloid malignancies receiving myelosuppressive anti-cancer drugs associated with a clinically significant incidence of febrile neutropenia [see Clinical Studies (14.1)].

Limitations of Use

Fulphila is not indicated for the mobilization of peripheral blood progenitor cells for hematopoietic stem cell transplantation.

2 DOSAGE AND ADMINISTRATION

2.1 Patients with Cancer Receiving Myelosuppressive Chemotherapy

The recommended dosage of Fulphila is a single subcutaneous injection of 6 mg administered once per chemotherapy cycle. For dosing in pediatric patients weighing less than 45 kg, refer to Table 1. Do not administer Fulphila between 14 days before and 24 hours after administration of cytotoxic chemotherapy.

2.2 Administration

Fulphila is administered subcutaneously via a single-dose prefilled syringe for manual use.

Prior to use‚ remove the carton from the refrigerator and allow the Fulphila prefilled syringe to reach room temperature for a minimum of 30 minutes. Discard any prefilled syringe left at room temperature for greater than 72 hours.

Parenteral drug products should be inspected visually for particulate matter and discoloration prior to administration, whenever solution and container permit. Do not administer Fulphila if discoloration or particulates are observed.

Pediatric Patients weighing less than 45 kg

The Fulphila prefilled syringe is not designed to allow for direct administration of doses less than 0.6 mL (6 mg). The syringe does not bear graduation marks, which are necessary to accurately measure doses of Fulphila less than 0.6 mL (6 mg) for direct administration to patients. Thus, the direct administration to patients requiring dosing of less than 0.6 mL (6 mg) is not recommended due to the potential for dosing errors. Refer to Table 1.

Table 1. Dosing of Fulphila for pediatric patients weighing less than 45 kg
Body Weight | Fulphila Dose | Volume to Administer
Less than 10 kg [For pediatric patients weighing less than 10 kg, administer 0.1 mg/kg (0.01 mL/kg) of Fulphila.] | See below | See below
10 to 20 kg | 1.5 mg | 0.15 mL
21 to 30 kg | 2.5 mg | 0.25 mL
31 to 44 kg | 4 mg | 0.4 mL

3 DOSAGE FORMS AND STRENGTHS

Fulphila is a clear, colorless, preservative-free solution available as:

- Injection: 6 mg/0.6 mL in a single-dose prefilled syringe for manual use only.

4 CONTRAINDICATIONS

Fulphila is contraindicated in patients with a history of serious allergic reactions to pegfilgrastim products or filgrastim products. Reactions have included anaphylaxis [see Warnings and Precautions (5.3)].

5 WARNINGS AND PRECAUTIONS

5.1 Splenic Rupture

Splenic rupture, including fatal cases, can occur following the administration of pegfilgrastim products. Evaluate for an enlarged spleen or splenic rupture in patients who report left upper abdominal or shoulder pain after receiving Fulphila.

5.2 Acute Respiratory Distress Syndrome

Acute respiratory distress syndrome (ARDS) can occur in patients receiving pegfilgrastim products. Evaluate patients who develop fever and lung infiltrates or respiratory distress after receiving Fulphila, for ARDS. Discontinue Fulphila in patients with ARDS.

5.3 Serious Allergic Reactions

Serious allergic reactions, including anaphylaxis, can occur in patients receiving pegfilgrastim products. The majority of reported events occurred upon initial exposure. Allergic reactions, including anaphylaxis, can recur within days after the discontinuation of initial anti-allergic treatment. Permanently discontinue Fulphila in patients with serious allergic reactions. Do not administer Fulphila to patients with a history of serious allergic reactions to pegfilgrastim products or filgrastim products.

5.4 Use in Patients with Sickle Cell Disorders

Severe and sometimes fatal sickle cell crises can occur in patients with sickle cell disorders receiving pegfilgrastim products. Discontinue Fulphila if sickle cell crisis occurs.

5.5 Glomerulonephritis

Glomerulonephritis has occurred in patients receiving pegfilgrastim. The diagnoses were based upon azotemia, hematuria (microscopic and macroscopic), proteinuria, and renal biopsy. Generally, events of glomerulonephritis resolved after dose reduction or discontinuation of pegfilgrastim. If glomerulonephritis is suspected, evaluate for cause. If causality is likely, consider dose-reduction or interruption of Fulphila.

5.6 Leukocytosis

White blood cell (WBC) counts of 100 x 109/L or greater have been observed in patients receiving pegfilgrastim products. Monitoring of complete blood count (CBC) during Fulphila therapy is recommended.

5.7 Thrombocytopenia

Thrombocytopenia has been reported in patients receiving pegfilgrastim. Monitor platelet counts.

5.8 Capillary Leak Syndrome

Capillary leak syndrome has been reported after G-CSF administration, including pegfilgrastim, and is characterized by hypotension, hypoalbuminemia, edema and hemoconcentration. Episodes vary in frequency, severity and may be life-threatening if treatment is delayed. Patients who develop symptoms of capillary leak syndrome should be closely monitored and receive standard symptomatic treatment, which may include a need for intensive care.

5.9 Potential for Tumor Growth Stimulatory Effects on Malignant Cells

The granulocyte colony-stimulating factor (G-CSF) receptor through which pegfilgrastim products and filgrastim products act has been found on tumor cell lines. The possibility that pegfilgrastim products act as a growth factor for any tumor type, including myeloid malignancies and myelodysplasia, diseases for which pegfilgrastim products are not approved, cannot be excluded.

5.10 Myelodysplastic Syndrome (MDS) and Acute Myeloid Leukemia (AML) in Patients with Breast and Lung Cancer

MDS and AML have been associated with the use of pegfilgrastim in conjunction with chemotherapy and/or radiotherapy in patients with breast and lung cancer. Monitor patients for signs and symptoms of MDS/AML in these settings.

5.11 Aortitis

Aortitis has been reported in patients receiving pegfilgrastim. It may occur as early as the first week after start of therapy. Manifestations may include generalized signs and symptoms such as fever, abdominal pain, malaise, back pain, and increased inflammatory markers (e.g., c-reactive protein and white blood cell count). Consider aortitis in patients who develop these signs and symptoms without known etiology. Discontinue Fulphila if aortitis is suspected.

5.12 Nuclear Imaging

Increased hematopoietic activity of the bone marrow in response to growth factor therapy has been associated with transient positive bone imaging changes. This should be considered when interpreting bone imaging results.

6 ADVERSE REACTIONS

The following clinically significant adverse reactions are discussed in greater detail in other sections of the labeling:

- Splenic Rupture [See Warnings and Precautions (5.1)]
- Acute Respiratory Distress Syndrome [See Warnings and Precautions (5.2)]
- Serious Allergic Reactions [See Warnings and Precautions (5.3)]
- Use in Patients with Sickle Cell Disorders [See Warnings and Precautions (5.4)]
- Glomerulonephritis [See Warnings and Precautions (5.5)]
- Leukocytosis [See Warnings and Precautions (5.6)]
- Thrombocytopenia [See Warnings and Precautions (5.7)]
- Capillary Leak Syndrome [See Warnings and Precautions (5.8)]
- Potential for Tumor Growth Stimulatory Effects on Malignant Cells [See Warnings and Precautions (5.9)]
- Myelodysplastic syndrome [See Warnings and Precautions (5.10)]
- Acute myeloid leukemia [See Warnings and Precautions (5.10)]
- Aortitis [see Warnings and Precautions (5.11)]

6.1 Clinical Trials Experience

Because clinical trials are conducted under widely varying conditions, adverse reaction rates observed in the clinical trials of a drug cannot be directly compared with rates in the clinical trials of another drug and may not reflect the rates observed in clinical practice.

Pegfilgrastim clinical trials safety data are based upon 932 patients receiving pegfilgrastim in seven randomized clinical trials. The population was 21 to 88 years of age and 92% female. The ethnicity was 75% Caucasian, 18% Hispanic, 5% Black, and 1% Asian. Patients with breast (n = 823), lung and thoracic tumors (n = 53) and lymphoma (n = 56) received pegfilgrastim after nonmyeloablative cytotoxic chemotherapy. Most patients received a single 100 mcg/kg (n = 259) or a single 6 mg (n = 546) dose per chemotherapy cycle over 4 cycles.

The following adverse reaction data in Table 2 are from a randomized, double-blind, placebo-controlled study in patients with metastatic or non-metastatic breast cancer receiving docetaxel 100 mg/m^2 every 21 days (Study 3). A total of 928 patients were randomized to receive either 6 mg pegfilgrastim (n = 467) or placebo (n = 461). The patients were 21 to 88 years of age and 99% female. The ethnicity was 66% Caucasian, 31% Hispanic, 2% Black, and < 1% Asian, Native American, or other.

The most common adverse reactions occurring in ≥ 5% of patients and with a between-group difference of ≥ 5% higher in the pegfilgrastim arm in placebo-controlled clinical trials are bone pain and pain in extremity.

Table 2. Adverse Reactions with ≥ 5% Higher Incidence in Pegfilgrastim Patients Compared to Placebo in Study 3
Body System; Adverse Reaction | Placebo; (N = 461) | Pegfilgrastim 6 mg SC on Day 2; (N = 467)
Musculoskeletal and connective tissue disorders
Bone pain | 26% | 31%
Pain in extremity | 4% | 9%

Leukocytosis

In clinical studies, leukocytosis (WBC counts > 100 x 10^9/L) was observed in less than 1% of 932 patients with non-myeloid malignancies receiving pegfilgrastim. No complications attributable to leukocytosis were reported in clinical studies.

6.2 Immunogenicity

As with all therapeutic proteins, there is a potential for immunogenicity. The detection of antibody formation is highly dependent on the sensitivity and specificity of the assay. Additionally, the observed incidence of antibody (including neutralizing antibody) positivity in an assay may be influenced by several factors, including assay methodology, sample handling, timing of sample collection, concomitant medications, and underlying disease. For these reasons, comparison of the incidence of antibodies in the studies described below with the incidence of antibodies in other studies or to other pegfilgrastim products may be misleading.

Binding antibodies to pegfilgrastim were detected using a BIAcore assay. The approximate limit of detection for this assay is 500 ng/mL. Pre-existing binding antibodies were detected in approximately 6% (51/849) of patients with metastatic breast cancer. Four of 521 pegfilgrastim-treated subjects who were negative at baseline developed binding antibodies to pegfilgrastim following treatment. None of these 4 patients had evidence of neutralizing antibodies detected using a cell-based bioassay.

6.3 Postmarketing Experience

The following adverse reactions have been identified during post approval use of pegfilgrastim products. Because these reactions are reported voluntarily from a population of uncertain size, it is not always possible to reliably estimate their frequency or establish a causal relationship to drug exposure.

- Splenic rupture and splenomegaly (enlarged spleen) [see Warnings and Precautions (5.1)]
- Acute respiratory distress syndrome (ARDS) [see Warnings and Precautions (5.2)]
- Allergic reactions/hypersensitivity, including anaphylaxis, skin rash, and urticaria, generalized erythema, and flushing [see Warnings and Precautions (5.3)]
- Sickle cell crisis [see Warnings and Precautions (5.4)]
- Glomerulonephritis [see Warnings and Precautions (5.5)]
- Leukocytosis [see Warnings and Precautions (5.6)]
- Thrombocytopenia [see Warnings and Precautions (5.7)]
- Capillary Leak Syndrome [see Warnings and Precautions (5.8)]
- Injection site reactions
- Sweet’s syndrome, (acute febrile neutrophilic dermatosis), cutaneous vasculitis
- Myelodysplastic syndrome (MDS) and acute myeloid leukemia (AML) in patients with breast and lung cancer receiving chemotherapy and/or radiotherapy [see Warnings and Precautions (5.10)]
- Aortitis [see Warnings and Precautions (5.11)]
- Alveolar hemorrhage

8 USE IN SPECIFIC POPULATIONS

8.1 Pregnancy

Risk Summary

Although available data with Fulphila or pegfilgrastim product use in pregnant women are insufficient to establish whether there is a drug associated risk of major birth defects, miscarriage, or adverse maternal or fetal outcomes, there are available data from published studies in pregnant women exposed to filgrastim products. These studies have not established an association of filgrastim product use during pregnancy with major birth defects, miscarriage or adverse maternal or fetal outcomes.

In animal studies, no evidence of reproductive/developmental toxicity occurred in the offspring of pregnant rats that received cumulative doses of pegfilgrastim approximately 10 times the recommended human dose (based on body surface area). In pregnant rabbits, increased embryolethality and spontaneous abortions occurred at 4 times the maximum recommended human dose simultaneously with signs of maternal toxicity (see Data).

The estimated background risk of major birth defects and miscarriage for the indicated population is unknown. All pregnancies have a background risk of birth defect, loss, or other adverse outcomes. In the U.S. general population, the estimated background risk of major birth defects and miscarriage in clinically recognized pregnancies is 2-4% and 15-20%, respectively.

Data

Human Data

Retrospective studies indicate that exposure to pegfilgrastim is without significant adverse effect on fetal outcomes and neutropenia. Preterm deliveries have been reported in some patients.

Animal Data

Pregnant rabbits were dosed with pegfilgrastim subcutaneously every other day during the period of organogenesis. At cumulative doses ranging from the approximate human dose to approximately 4 times the recommended human dose (based on body surface area), the treated rabbits exhibited decreased maternal food consumption, maternal weight loss, as well as reduced fetal body weights and delayed ossification of the fetal skull; however, no structural anomalies were observed in the offspring from either study. Increased incidences of post-implantation losses and spontaneous abortions (more than half the pregnancies) were observed at cumulative doses approximately 4 times the recommended human dose, which were not seen when pregnant rabbits were exposed to the recommended human dose.

Three studies were conducted in pregnant rats dosed with pegfilgrastim at cumulative doses up to approximately 10 times the recommended human dose at the following stages of gestation: during the period of organogenesis, from mating through the first half of pregnancy, and from the first trimester through delivery and lactation. No evidence of fetal loss or structural malformations was observed in any study. Cumulative doses equivalent to approximately 3 and 10 times the recommended human dose resulted in transient evidence of wavy ribs in fetuses of treated mothers (detected at the end of gestation but no longer present in pups evaluated at the end of lactation).

8.2 Lactation

Risk Summary

There are no data on the presence of pegfilgrastim products in human milk, the effects on the breastfed child, or the effects on milk production. Other filgrastim products are secreted poorly into breast milk, and filgrastim products are not absorbed orally by neonates. The developmental and health benefits of breastfeeding should be considered along with the mother’s clinical need for Fulphila and any potential adverse effects on the breastfed child from Fulphila or from the underlying maternal condition.

8.4 Pediatric Use

The safety and effectiveness of pegfilgrastim have been established in pediatric patients. No overall differences in safety were identified between adult and pediatric patients based on postmarketing surveillance and review of the scientific literature.

Use of pegfilgrastim in pediatric patients for chemotherapy-induced neutropenia is based on adequate and well-controlled studies in adults with additional pharmacokinetic and safety data in pediatric patients with sarcoma [see Clinical Pharmacology (12.3) and Clinical Studies (14.1)].

8.5 Geriatric Use

Of the 932 patients with cancer who received pegfilgrastim in clinical studies, 139 (15%) were aged 65 and over, and 18 (2%) were aged 75 and over. No overall differences in safety or effectiveness were observed between patients aged 65 and older and younger patients.

10 OVERDOSAGE

Overdosage of pegfilgrastim products may result in leukocytosis and bone pain. Events of edema, dyspnea, and pleural effusion have been reported in a single patient who administered pegfilgrastim on 8 consecutive days in error. In the event of overdose, the patient should be monitored for adverse reactions [see Adverse Reactions (6)].

11 DESCRIPTION

Pegfilgrastim-jmdb is a covalent conjugate of recombinant methionyl human G-CSF and monomethoxypolyethylene glycol. Recombinant methionyl human G-CSF is a water-soluble 175 amino acid protein with a molecular weight of approximately 19 kilodaltons (kD). Recombinant methionyl human G-CSF is obtained from the bacterial fermentation of a strain of E coli transformed with a genetically engineered plasmid containing the human G-CSF gene. To produce pegfilgrastim-jmdb a 20 kD monomethoxypolyethylene glycol molecule is covalently bound to the N-terminal methionyl residue of recombinant methionyl human G-CSF. The average molecular weight of pegfilgrastim-jmdb is approximately 39 kD.

Fulphila (pegfilgrastim-jmdb) injection is intended for subcutaneous use only and is supplied in a single-dose prefilled syringe with a 29 gauge needle, with UltraSafe Passive Plus™ Needle Guard. The prefilled syringe does not bear graduation marks and is designed to deliver the entire contents of the syringe (6 mg/0.6 mL).

The delivered 0.6 mL dose from the prefilled syringe contains 6 mg pegfilgrastim-jmdb (based on protein mass only) in a sterile, clear, colorless, preservative-free solution (pH 4.0) containing acetate (0.7 mg), D-sorbitol (30 mg), polysorbate 20 (0.024 mg) and sodium (0.01 mg) in Water for Injection, USP.

12 CLINICAL PHARMACOLOGY

12.1 Mechanism of Action

Pegfilgrastim products are colony-stimulating factors that act on hematopoietic cells by binding to specific cell surface receptors, thereby stimulating proliferation, differentiation, commitment, and end cell functional activation.

12.2 Pharmacodynamics

Animal data and clinical data in humans suggest a correlation between pegfilgrastim products exposure and the duration of severe neutropenia as a predictor of efficacy. Selection of the dosing regimen of Fulphila is based on reducing the duration of severe neutropenia.

12.3 Pharmacokinetics

The pharmacokinetics of pegfilgrastim was studied in 379 patients with cancer. The pharmacokinetics of pegfilgrastim was nonlinear, and clearance decreased with increases in dose. Neutrophil receptor binding is an important component of the clearance of pegfilgrastim, and serum clearance is directly related to the number of neutrophils. In addition to numbers of neutrophils, body weight appeared to be a factor. Patients with higher body weights experienced higher systemic exposure to pegfilgrastim after receiving a dose normalized for body weight. A large variability in the pharmacokinetics of pegfilgrastim was observed. The half-life of pegfilgrastim ranged from 15 to 80 hours after subcutaneous injection.

Specific Populations

No gender-related differences were observed in the pharmacokinetics of pegfilgrastim, and no differences were observed in the pharmacokinetics of geriatric patients (≥ 65 years of age) compared with younger patients (< 65 years of age) [see Use in Specific Populations (8.5)].

Patients with Renal Impairment

In a study of 30 subjects with varying degrees of renal dysfunction, including end stage renal disease, renal dysfunction had no effect on the pharmacokinetics of pegfilgrastim.

Pediatric Patients with Cancer Receiving Myelosuppressive Chemotherapy

The pharmacokinetics and safety of pegfilgrastim were studied in 37 pediatric patients with sarcoma in Study 4 [see Clinical Studies 14.1]. The mean (± standard deviation [SD]) systemic exposure (AUC0-inf) of pegfilgrastim after subcutaneous administration at 100 mcg/kg was 47.9 (± 22.5) mcg·hr/mL in the youngest age group (0 to 5 years, n = 11), 22.0 (± 13.1) mcg·hr/mL in the (6 to 11 years age group (n = 10), and 29.3 (± 23.2) mcg·hr/mL in the 12 to 21 years age group (n = 13). The terminal elimination half-lives of the corresponding age groups were 30.1 (± 38.2) hours, 20.2 (± 11.3) hours, and 21.2 (± 16.0) hours, respectively.

13 NONCLINICAL TOXICOLOGY

13.1 Carcinogenesis, Mutagenesis, Impairment of Fertility

No carcinogenicity or mutagenesis studies have been performed with pegfilgrastim products.

Pegfilgrastim did not affect reproductive performance or fertility in male or female rats at cumulative weekly doses approximately 6 to 9 times higher than the recommended human dose (based on body surface area).

14 CLINICAL STUDIES

14.1 Patients with Cancer Receiving Myelosuppressive Chemotherapy

Pegfilgrastim was evaluated in three randomized, double-blind, controlled studies. Studies 1 and 2 were active-controlled studies that employed doxorubicin 60 mg/m^2 and docetaxel 75 mg/m^2 administered every 21 days for up to 4 cycles for the treatment of metastatic breast cancer. Study 1 investigated the utility of a fixed dose of pegfilgrastim. Study 2 employed a weight-adjusted dose. In the absence of growth factor support, similar chemotherapy regimens have been reported to result in a 100% incidence of severe neutropenia (ANC < 0.5 x 10^9/L) with a mean duration of 5 to 7 days and a 30% to 40% incidence of febrile neutropenia. Based on the correlation between the duration of severe neutropenia and the incidence of febrile neutropenia found in studies with filgrastim, duration of severe neutropenia was chosen as the primary endpoint in both studies, and the efficacy of pegfilgrastim was demonstrated by establishing comparability to filgrastim-treated patients in the mean days of severe neutropenia.

In Study 1, 157 patients were randomized to receive a single subcutaneous injection of pegfilgrastim (6 mg) on day 2 of each chemotherapy cycle or daily subcutaneous filgrastim (5 mcg/kg/day) beginning on day 2 of each chemotherapy cycle. In Study 2, 310 patients were randomized to receive a single subcutaneous injection of pegfilgrastim (100 mcg/kg) on day 2 or daily subcutaneous filgrastim (5 mcg/kg/day) beginning on day 2 of each chemotherapy cycle.

Both studies met the major efficacy outcome measure of demonstrating that the mean days of severe neutropenia of pegfilgrastim-treated patients did not exceed that of filgrastim-treated patients by more than 1 day in cycle 1 of chemotherapy. The mean days of cycle 1 severe neutropenia in Study 1 were 1.8 days in the pegfilgrastim arm compared to 1.6 days in the filgrastim arm [difference in means 0.2 (95% CI -0.2, 0.6)] and in Study 2 were 1.7 days in the pegfilgrastim arm compared to 1.6 days in the filgrastim arm [difference in means 0.1 (95% CI -0.2, 0.4)].

A secondary endpoint in both studies was days of severe neutropenia in cycles 2 through 4 with results similar to those for cycle 1.

Study 3 was a randomized, double-blind, placebo-controlled study that employed docetaxel 100 mg/m^2 administered every 21 days for up to 4 cycles for the treatment of metastatic or non-metastatic breast cancer. In this study, 928 patients were randomized to receive a single subcutaneous injection of pegfilgrastim (6 mg) or placebo on day 2 of each chemotherapy cycle. Study 3 met the major trial outcome measure of demonstrating that the incidence of febrile neutropenia (defined as temperature ≥ 38.2°C and ANC ≤ 0.5 x10^9/L) was lower for pegfilgrastim-treated patients as compared to placebo-treated patients (1% versus 17%, respectively, p < 0.001). The incidence of hospitalizations (1% versus 14%) and IV anti-infective use (2% versus 10%) for the treatment of febrile neutropenia was also lower in the pegfilgrastim-treated patients compared to the placebo-treated patients.

Study 4 was a multicenter, randomized, open-label study to evaluate the efficacy, safety, and pharmacokinetics [see Clinical Pharmacology (12.3)] of pegfilgrastim in pediatric and young adult patients with sarcoma. Patients with sarcoma receiving chemotherapy age 0 to 21 years were eligible. Patients were randomized to receive subcutaneous pegfilgrastim as a single-dose of 100 mcg/kg (n = 37) or subcutaneous filgrastim at a dose 5 mcg/kg/day (n = 6) following myelosuppressive chemotherapy. Recovery of neutrophil counts was similar in the pegfilgrastim and filgrastim groups. The most common adverse reaction reported was bone pain.

16 HOW SUPPLIED/STORAGE AND HANDLING

Fulphila single-dose prefilled syringe for manual use

Fulphila (pegfilgrastim-jmdb) Injection is a clear, colorless solution supplied in a prefilled single-dose syringe for manual use containing 6 mg pegfilgrastim-jmdb, supplied with a 29 gauge, 1/2-inch needle with an UltraSafe Passive Plus™ Needle Guard.

Fulphila is provided in a dispensing pack containing one sterile 6 mg/0.6 mL prefilled syringe.

NDC 83257-005-41

Fulphila prefilled syringe does not bear graduation marks and is intended only to deliver the entire contents of the syringe (6 mg/0.6 mL) for direct administration. Use of the prefilled syringe is not recommended for direct administration for pediatric patients weighing less than 45 kg who require doses that are less than the full contents of the syringe.

Store refrigerated between 2° to 8°C (36° to 46°F) in the carton to protect from light or physical damage. Do not shake. Discard syringes stored at room temperature for more than 72 hours. Avoid freezing; if frozen, thaw in the refrigerator before administration. Discard syringe if frozen more than once.

17 PATIENT COUNSELING INFORMATION

Advise the patient to read the FDA-approved patient labeling (Patient Information and Instructions for Use).

Advise patients of the following risks and potential risks with Fulphila:

- Splenic rupture and splenomegaly [see Warnings and Precautions (5.1)]
- Acute Respiratory Distress Syndrome [see Warnings and Precautions (5.2)]
- Serious allergic reactions [see Warnings and Precautions (5.3)]
- Sickle cell crisis [see Warnings and Precautions (5.4)]
- Glomerulonephritis [see Warnings and Precautions (5.5)]
- Increased risk of Myelodysplastic Syndrome and/or Acute Myeloid Leukemia in patients with breast and lung cancer who receive pegfilgrastim in conjunction with chemotherapy and/or radiation therapy [see Warnings and Precautions (5.10)]
- Capillary Leak Syndrome [see Warnings and Precautions (5.8)]
- Aortitis [see Warnings and Precautions (5.11)]

Instruct patients who self-administer Fulphila using the single-dose prefilled syringe of the:

- Importance of following the Instructions for Use.
- Dangers of reusing syringes.
- Importance of following local requirements for proper disposal of used syringes.

Manufactured by:
Biocon Biologics Inc.
245 Main st, 2nd Floor
Cambridge, MA 02142 U.S.A.
U.S. License No. 2324

Patient Information

Fulphila® (FULL-fil-ah)
(pegfilgrastim-jmdb)
Injection
Single-Dose Prefilled Syringe

What is Fulphila?

Fulphila is a man-made form of granulocyte colony-stimulating factor (G-CSF). G-CSF is a substance produced by the body. It stimulates the growth of neutrophils, a type of white blood cell important in the body’s fight against infection.

Do not take Fulphila if you have had a serious allergic reaction to pegfilgrastim products or filgrastim products.

Before you receive Fulphila, tell your healthcare provider about all of your medical conditions, including if you:

- have a sickle cell disorder.
- have kidney problems.
- are pregnant or plan to become pregnant. It is not known if Fulphila will harm your unborn baby.
- are breastfeeding or plan to breastfeed. It is not known if Fulphila passes into your breast milk.

Tell your healthcare provider about all of the medicines you take, including prescription and over-the-counter medicines, vitamins, and herbal supplements.

How will I receive Fulphila?

- Fulphila is given as an injection under your skin (subcutaneous injection) by a healthcare provider. If your healthcare provider decides that the subcutaneous injections can be given at home by you or your caregiver, follow the detailed “Instructions for Use” that comes with your Fulphila for information on how to prepare and inject a dose of Fulphila.
- You and your caregiver will be shown how to prepare and inject Fulphila before you use it.
- You should not inject a dose of Fulphila to children weighing less than 45 kg from a Fulphila prefilled syringe. A dose less than 0.6 mL (6 mg) cannot be accurately measured using the Fulphila prefilled syringe.
- If you are receiving Fulphila because you are also receiving chemotherapy, the last dose of Fulphila should be injected at least 14 days before and 24 hours after your dose of chemotherapy.
- If you miss a dose of Fulphila, talk to your healthcare provider about when you should give your next dose.

What are possible side effects of Fulphila?

Fulphila may cause serious side effects, including:

- Spleen rupture. Your spleen may become enlarged and can rupture. A ruptured spleen can cause death. Call your healthcare provider right away if you have pain in the left upper stomach area or your left shoulder.
- A serious lung problem called Acute Respiratory Distress Syndrome (ARDS). Call your healthcare provider or get emergency care right away if you have shortness of breath with or without a fever, trouble breathing, or a fast rate of breathing.
- Serious allergic reactions. Fulphila can cause serious allergic reactions. These reactions can cause a rash over your whole body, shortness of breath, wheezing, dizziness, swelling around your mouth or eyes, fast heart rate, and sweating. If you have any of these symptoms, stop using Fulphila and call your healthcare provider or get emergency medical help right away.
- Sickle cell crises. You may have a serious sickle cell crisis if you have a sickle cell disorder and receive Fulphila. Serious sickle cell crises have happened in people with sickle cell disorders receiving pegfilgrastim that has sometimes led to death. Call your healthcare provider right away if you have symptoms of sickle cell crisis such as pain or difficulty breathing.
- Kidney injury (glomerulonephritis). Fulphila can cause kidney injury. Call your healthcare provider right away if you develop any of the following symptoms:
  - swelling of your face or ankles
  - blood in your urine or dark colored urine
  - you urinate less than usual
- Increased white blood cell count (leukocytosis). Your healthcare provider will check your blood during treatment with Fulphila.
- Decreased platelet count (thrombocytopenia). Your healthcare provider will check your blood during treatment with Fulphila. Tell your healthcare provider if you have unusual bleeding or bruising during treatment with Fulphila. This could be a sign of decreased platelet counts, which may reduce the ability of your blood to clot.
- Capillary Leak Syndrome. Fulphila can cause fluid to leak from blood vessels into your body’s tissues. This condition is called “Capillary Leak Syndrome” (CLS). CLS can quickly cause you to have symptoms that may become life-threatening. Get emergency medical help right away if you develop any of the following symptoms:
  - swelling or puffiness and are urinating less than usual
  - trouble breathing
  - swelling of your stomach-area (abdomen) and feeling of fullness
  - dizziness or feeling faint
  - a general feeling of tiredness
- Myelodysplastic syndrome and acute myeloid leukemia. If you have breast cancer or lung cancer, when Fulphila is used with chemotherapy and radiation therapy, or with radiation therapy alone, you may have an increased risk of developing a precancerous blood condition called myelodysplastic syndrome (MDS) or a blood cancer called acute myeloid leukemia (AML). Symptoms of MDS and AML may include tiredness, fever, and easy bruising or bleeding. Call your healthcare provider if you develop these symptoms during treatment with Fulphila
- Inflammation of the aorta (aortitis). Inflammation of the aorta (the large blood vessel which transports blood from the heart to the body) has been reported in patients who received pegfilgrastim. Symptoms may include fever, abdominal pain, feeling tired, and back pain. Call your healthcare provider if you experience these symptoms.

The most common side effects of Fulphila are pain in the bones, arms, and legs.

These are not all the possible side effects of Fulphila.

Call your health care provider for medical advice about side effects. You may report side effects to FDA at 1-800-FDA-1088.

How should I store Fulphila?

- Store Fulphila in the refrigerator between 36°F to 46°F (2°C to 8°C).
- Take Fulphila out of the refrigerator 30 minutes before use and allow it to reach room temperature before preparing an injection.
- Avoid freezing. If Fulphila is accidently frozen, allow the prefilled syringe to thaw in the refrigerator before injecting.
- Do not use a Fulphila prefilled syringe that has been frozen more than 1 time. Use a new Fulphila prefilled syringe.
- Keep the prefilled syringe in the original carton to protect from light or physical damage.
- Do not shake the prefilled syringe.
- Throw away (dispose of) any Fulphila that has been left at room temperature, 68°F to 77ºF (20°C to 25ºC) for more than 72 hours or frozen more than 1 time.

Keep the Fulphila prefilled syringe out of the reach of children.

General information about the safe and effective use of Fulphila.

Medicines are sometimes prescribed for purposes other than those listed in a Patient Information leaflet. Do not use Fulphila for a condition for which it was not prescribed. Do not give Fulphila to other people, even if they have the same symptoms that you have. It may harm them. You can ask your pharmacist or healthcare provider for information about Fulphila that is written for health professionals.

What are the ingredients in Fulphila?

Active ingredient: pegfilgrastim-jmdb

Inactive ingredients: acetate, D-sorbitol, polysorbate 20, and sodium in Water for Injection.

Manufactured by: Biocon Biologics Inc.

245 Main st, 2nd Floor Cambridge, MA 02142 U.S.A

U.S. License No. 2324

Product of India. Code No.: KR/DRUGS/KTK/28D/07/2006

For more information, go to www.fulphila.com or call 1-833-986-1468.

This Patient Information has been approved by the U.S. Food and Drug Administration. Revised: 06/2023

FULPHILA® is a registered trademark of Biosimilars New Co Ltd; a Biocon Biologics Company.

Copyright © 2023 Biocon Biologics Inc. All rights reserved

Manufactured by:
Biocon Biologics Inc.
245 Main st. 2nd Floor
Cambridge, MA 02142 U.S.A.
U.S. License No. 2324

Product of India

KR/DRUGS/KTK/28D/07/2006

Revised: 06/2023

BF1639/05

Instructions for Use

FULPHILA® (FULL-fil-ah)

(pegfilgrastim-jmdb)

injection, for subcutaneous use

Single-Dose Prefilled Syringe

Guide to Parts

Before Use

After Use

Important: The needle is covered by the gray needle cap before use.

Important Information

Read the Patient Information for important information you need to know about Fulphila before using these Instructions for Use.

Storing the Fulphila prefilled syringe

- Store Fulphila in the refrigerator between 36ºF to 46ºF (2ºC to 8ºC).
- Take Fulphila out of the refrigerator 30 minutes before use and allow it to reach room temperature before preparing an injection.
- Avoid freezing. If Fulphila is accidentally frozen, allow the prefilled syringe to thaw in the refrigerator before injecting.
- Do not use a Fulphila prefilled syringe that has been frozen more than 1 time. Use a new Fulphila prefilled syringe.
- Throw away (dispose of) any Fulphila that has been left at room temperature, 68ºF to 77ºF (20ºC to 25ºC) for more than 72 hours or frozen more than 1 time. See Step 4: Disposing of used prefilled syringes.
- Keep the prefilled syringe in the original carton to protect from light or physical damage.
- For questions about storage, contact your healthcare provider or pharmacist.
- Keep the Fulphila prefilled syringe out of the reach of children.

Before you use a Fulphila prefilled syringe, read this important information:

- It is important that you do not try to give yourself the injection unless you have received training from your healthcare provider.
- The prefilled syringe has a needle safety guard that will be activated to cover the needle after the injection is given. The needle safety guard will help prevent needlestick injuries to anyone who handles the prefilled syringe after the injection has been given.
- Make sure that the name Fulphila appears on the carton and prefilled syringe label.
  Fulphila is given as an injection into the tissue just under the skin (subcutaneous injection).
- You should not inject a dose of Fulphila to children weighing less than 45 kg from a Fulphila prefilled syringe. A dose less than 0.6 mL (6 mg) cannot be accurately measured using the Fulphila prefilled syringe.
- Do not use a prefilled syringe after the expiration date on the label.
- Do not shake the prefilled syringe.
- Do not use the prefilled syringe if the carton is open or damaged.
- Do not remove the gray needle cap from the prefilled syringe until you are ready to inject.
- Do not use the prefilled syringe if it has been dropped on a hard surface. The syringe may be broken even if you cannot see the break. Use a new prefilled syringe.
- Do not attempt to activate the prefilled syringe prior to injection.
- Do not attempt to remove the needle safety guard from the prefilled syringe.
- Do not attempt to remove the label from the prefilled syringe barrel before injecting your dose of Fulphila.

Call your healthcare provider if you have any questions.

Step 1: Gather supplies

A - Find a clean, well-lit and flat work surface, such as a table.

B - Take the prefilled syringe carton out of the refrigerator and place it on your clean work surface. Allow it to reach room temperature for 30 minutes before giving an injection.

C - Remove the prefilled syringe tray from the carton.

D - Wash your hands thoroughly with soap and water.

E - Gather the supplies for the injection:

- 1 alcohol wipe
- 1 cotton ball or gauze pad
- 1 adhesive bandage
- an FDA-cleared sharps disposal container

Step 2: Prepare for injection

F - Open the tray by peeling away the cover. Grab the
needle safety guard to remove the prefilled
syringe from the tray.

For safety reasons:

- Do not grab the plunger rod.
- Do not grasp the gray needle cap.

G - Inspect the medicine and prefilled syringe.

Make sure the medicine in the prefilled syringe is clear and colorless.

Do not use the prefilled syringe if:

- The medicine is cloudy or discolored, or contains flakes or particles.
- The prefilled syringe has been dropped.
- Any part appears cracked or broken.
- The gray needle cap is missing or not securely attached.
- The expiration date printed on the label has
  passed.

In all cases, use a new prefilled syringe and call your healthcare provider.

H - Prepare and clean the injection site.
There are 4 injection sites that you can use:

- thigh
- stomach area (abdomen), except for a 2-inch area right around the navel (belly button)
- upper outer area of the buttocks (only if someone else is giving you the injection), and
- the outer area of the upper arm (only if someone else is giving you the injection).

Clean the injection site with an alcohol wipe. Let the skin dry.

- Do not touch this area again before injecting.
- Do not inject into areas where the skin is tender, bruised, red, or hard. Avoid injecting into areas with scars or stretch marks.
- If you want to use the same injection site, make sure it is not the same spot on the injection site you used for a previous injection.

I - Hold the prefilled syringe by the needle safety guard.
When ready, carefully pull the gray needle cap straight off and away from the body.

- Do not twist or bend the gray needle cap.
- Do not hold the prefilled syringe by the plunger rod.
- Do not put the gray needle cap back onto the prefilled syringe. Dispose of (throw away) the gray needle cap in your household trash.

Step 3: Inject the dose

J - Pinch the cleaned injection site to create a firm surface.

! Keep skin pinched
while injecting.

K - Hold the pinch. Insert the needle into the skin between 45 to 90 degrees.

- Do not touch the cleaned area
  of the skin

L - Using slow and constant pressure, push the plunger rod until it reaches the bottom.

! The plunger must be pushed fully in
order to inject the full dose.

M - Once the entire dose has been injected, the needle safety guard will be triggered. You can do either of the following:

- Release the plunger until the entire needle is covered and then remove the needle from the injection site.

or

- Gently remove the needle from the injection site and release the plunger until the entire needle is covered by the needle safety guard.

After releasing the plunger, the needle safety guard will safely cover the injection needle.

- Once the needle has been removed from the injection site, dispose of the syringe and needle in your sharps disposal container right away. See “Step 4: Disposing of used prefilled syringes”.
- If the needle safety guard is not activated or only partially activated, discard the product (without replacing the needle cap). See “Step 4: Disposing of used prefilled syringes”.
- If your injection is given by another person, they should also be careful when removing the needle from your skin in order to prevent accidental needlestick injury and possible infections.
- When you remove the syringe, if it looks like the medicine is still in the syringe barrel, this means you have not received the full dose. Call your healthcare provider right away.

N - Examine the injection site. If there is blood, press a cotton ball or gauze pad on the injection site. Do not rub the injection site. Apply an adhesive bandage if needed.

Step 4: Disposing of used prefilled syringes

- Put the used prefilled syringe in an FDA-cleared sharps disposal container right away after use. Do not throw away the syringe in the household trash.
- If you do not have an FDA-cleared sharps disposal container, you may use a household container that is:
  - made of heavy-duty plastic
  - can be closed with a tight-fitting, puncture-resistant lid without sharps being able to come out
  - upright and stable during use
  - leak-resistant
  - properly labeled to warn of hazardous waste inside the container
- When your sharps disposal container is almost full, you will need to follow your community guidelines for the right way to dispose of your sharps disposal container. There may be state or local laws about how you should throw away used needles and syringes. For more information about safe sharps disposal, and for specific information about sharps disposal in the state that you live in, go to the FDA’s website at http://www.fda.gov/safesharpsdisposal.

Important: Keep the sharps disposal container out of the reach of children.

- Do not reuse the prefilled syringe.
- Do not recycle prefilled syringes or throw them into household waste.

This Instructions for Use has been approved by the U.S. Food and Drug Administration.

Manufactured by:
Biocon Biologics Inc.
245 Main St, 2nd Floor
Cambridge, MA 02142, U.S.A.
U.S. License No. 2324

KR/DRUGS/KTK/28D/07/2006

Copyright © 2023 Biocon Biologics Inc. All rights reserved.

Revised: 06/2023

BF1638/05

PACKAGE/LABEL PRINCIPAL DISPLAY PANEL

NDC 83257-005-41 Rx only

Fulphila®
(pegfilgrastim-jmdb)
Injection
6 mg/0.6 mL

Single-Dose Prefilled Syringe

Pegylated Recombinant Methionyl Human Granulocyte Colony-Stimulating Factor (PEG-r-metHuG-CSF) derived from E Coli

For Subcutaneous Use Only

Sterile Solution - No Preservative

One 0.6 mL Single-Dose
Prefilled Syringe

Each 0.6 mL prefilled syringe contains: 6 mg pegfilgrastim (based on protein mass only) in a sterile, clear, colorless, preservative-free solution (pH 4.0) containing acetate (0.7 mg), D-sorbitol (30 mg), polysorbate 20 (0.024 mg), and sodium (0.01 mg) in water for injection, USP.

Store refrigerated at 2° to 8°C (36° to 46°F) in original carton to Protect from Light. Do Not Freeze or Shake.

Keep this and all medication out of the reach of children.

Dosage: See prescribing information for dosage and instructions for use.

Manufactured by:
Biocon Biologics Inc.
245 Main St, 2nd Floor
Cambridge, MA 02142, U.S.A.

U.S. License No. 2324

Product of India

KR/DRUGS/KTK/28D/07/2006

Copyright © 2023 Biocon Biologics Inc.

All rights reserved.